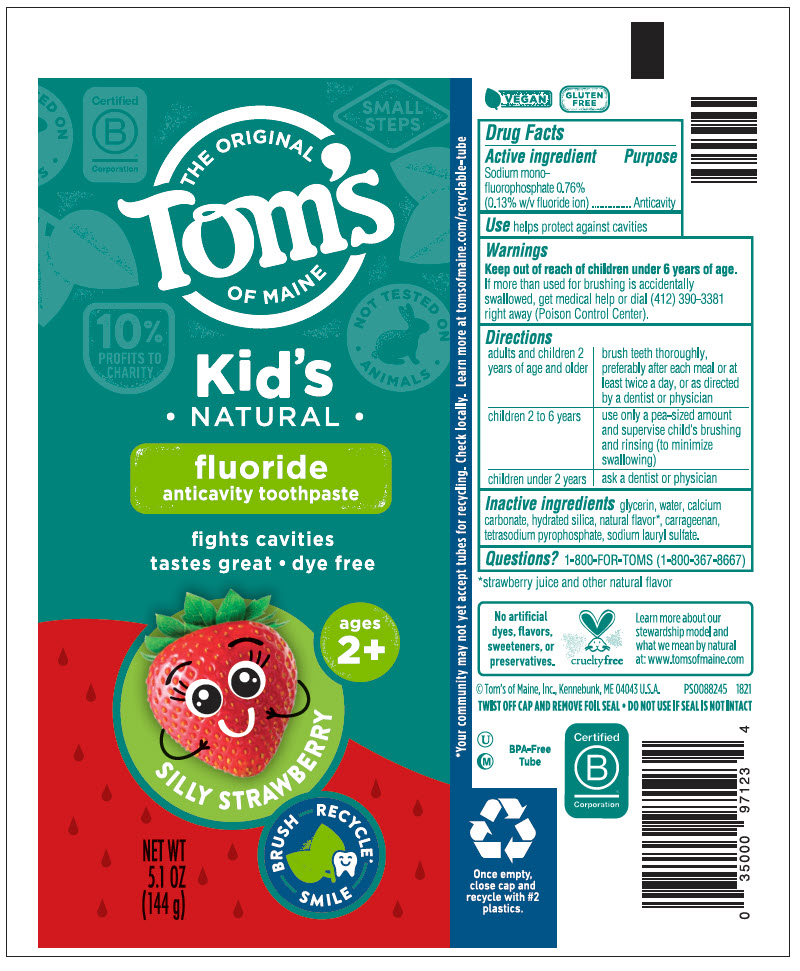 DRUG LABEL: Silly Strawberry Anticavity - BFT51 MRT
NDC: 51009-910 | Form: PASTE, DENTIFRICE
Manufacturer: Tom's of Maine, Inc.
Category: otc | Type: HUMAN OTC DRUG LABEL
Date: 20250812

ACTIVE INGREDIENTS: SODIUM MONOFLUOROPHOSPHATE 0.0014 g/1 g
INACTIVE INGREDIENTS: GLYCERIN; WATER; CALCIUM CARBONATE; HYDRATED SILICA; CARRAGEENAN; SODIUM PYROPHOSPHATE; SODIUM LAURYL SULFATE

Silly Strawberry Anticavity - BFT51 MRT

Drug Facts

Active ingredient

Sodium monofluorophosphate 0.76% (0.13% w/v fluoride ion)

Purpose

Anticavity

Use

helps protect against cavities

Warnings

Keep out of reach of children under 6 years of age. If more than used for brushing is accidentally swallowed, get medical help or dial (412) 390-3381 right away (Poison Control Center).

Directions

adults and children 2 years of age and older | brush teeth thoroughly, preferably after each meal or at least twice a day, or as directed by a dentist or physician
children 2 to 6 years | use only a pea-sized amount and supervise child's brushing and rinsing (to minimize swallowing)
children under 2 years | ask a dentist or physician

Inactive ingredients

glycerin, water, calcium carbonate, hydrated silica, natural flavor [strawberry juice and other natural flavor] , carrageenan, Tetrasodium Pyrophosphate, sodium lauryl sulfate

Questions?

1-800-FOR-TOMS (1-800-367-8667)

PRINCIPAL DISPLAY PANEL - 144 g Tube Label

THE ORIGINAL
Tom's
OF MAINE

Kid's
• NATURAL •

fluoride
anticavity toothpaste

fights cavities
tastes great • dye free

SILLY STRAWBERRY
ages
2+

NET WT
5.1 OZ
(144 g)

BRUSH RECYCLE*
SMILE